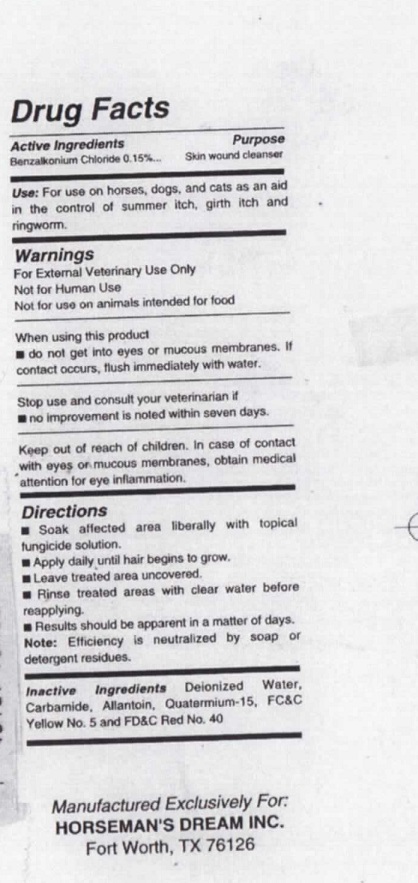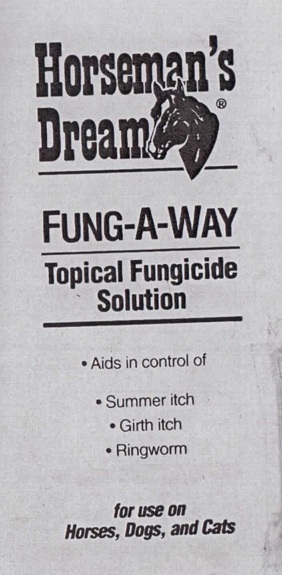 DRUG LABEL: HORSEMANS DREAM FUNG-A-WAY
NDC: 12090-1041 | Form: SOLUTION
Manufacturer: SUMMIT INDUSTRIES
Category: animal | Type: OTC ANIMAL DRUG LABEL
Date: 20100917

ACTIVE INGREDIENTS: BENZALKONIUM CHLORIDE 0.15 mL/100 mL
INACTIVE INGREDIENTS: WATER; UREA; ALLANTOIN; QUATERNIUM-15

HORSEMAN'S DREAM FUNG-A-WAY TOPICAL FUNGICIDE SOLUTION 16 oz

Drug Facts

Active Ingredients Purpose

Benzalkonium chloride 0.15% Skin wound cleaner

purpose: skin wound cleaner

Uses:

For use on horses, dogs, and cats, as an aid in the control of summer itch, girth itch and ringworm

Warnings

For external veterinary use only

Nor for human use

Not for use on animals intended for food

When using this product

do not get into eyes or mucous membranes. If contact occurs, flush immediately with water.

Stop use and consult your veterinarian if

no improvement is noted within seven days.

Keep out of reach of children. In case of contact with eyes or mucous membranes, obtain medical attention for eye inflammation.

Directions

soak affected area liberally with topical fungicide solution.

Apply daily until hair begins to grow.

Leave treated area uncovered

Rinse treated ares with clear water before reapplying

Results should be apparent in a matter of days

Note: efficiency is neutralized by soap or detergent residues.

Inactive Ingredients:

Deionized water, carbamide, allantoin, quaternium-15, FC and C yellow no. 5, FD and C red no. 40

PACKAGE LABEL

HORSEMAN'S DREAM

FUNG-A-WAY

Topical Fungicide Solution

-Aids in control of

-Summer itch

-girth itch-

-ringworm

for use on Horses, dogs, and cats

Manufactured Exclusively For:

Horseman's Dream Inc.

Forth Worth, TX 76126